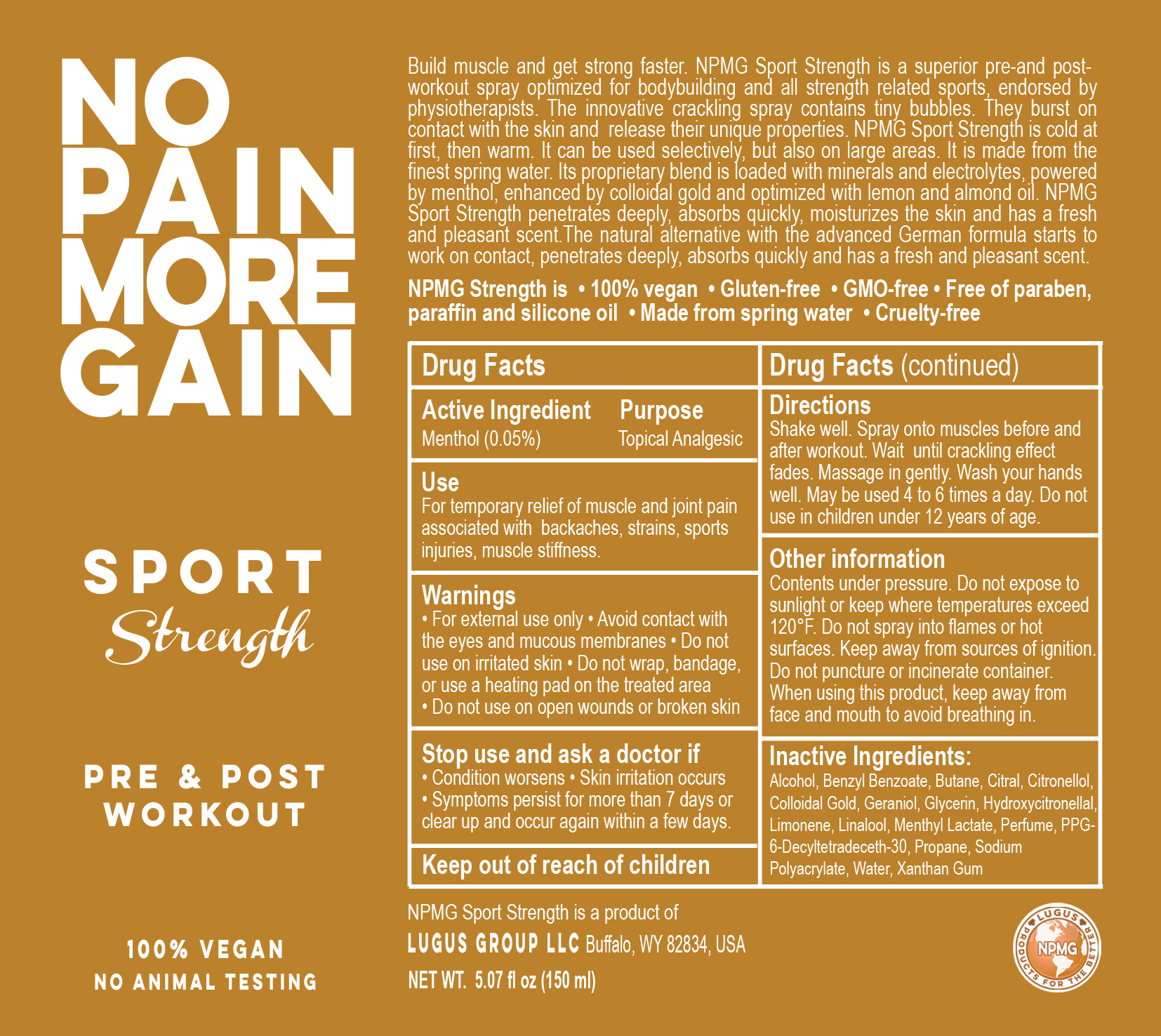 DRUG LABEL: No Pain More Gain
NDC: 69161-007 | Form: AEROSOL, SPRAY
Manufacturer: Lugus Group LLC
Category: otc | Type: HUMAN OTC DRUG LABEL
Date: 20191217

ACTIVE INGREDIENTS: MENTHOL 5 mg/100 mg
INACTIVE INGREDIENTS: LINALOOL, (+)-; HYDROXYCITRONELLAL; LIMONENE, (+)-; XANTHAN GUM; SODIUM POLYACRYLATE (2500000 MW); BENZYL BENZOATE; GERANIOL; WATER; ALCOHOL; PROPANE; GLYCERIN; MENTHYL LACTATE, (-)-; CITRAL; .BETA.-CITRONELLOL, (R)-; 2-BROMOBUTANE, (S)-; GOLD

Active Ingredient Menthol (0.05%)

Purpose Topical Analgesic

Use

For temporary relief of muscle and joint pain associated with backaches, strains, sports injuries, muscle stiffness.

Warnings

• For external use only • Avoid contact with the eyes and mucous membranes • Do not use on irritated skin • Do not wrap, bandage, or use a heating pad on the treated area • Do not use on open wounds or broken skin.

Stop use and ask a doctor if

• Condition worsens • skin irritation occurs • Symptoms persist for more than 7 days or clear up and occur again within a few days

Directions

Shake well. Spray onto muscles before and after workout. Wait until crackling effect fades. Massage in gently. Wash your hands well. May be used 4 to 6 times a day. Do not use in children under 12 years of age.

Other information

Contents under pressure. Do not expose to sunlight or keep where temperatures exceed 120°F. Do not spray into flames or hot surfaces. Keep away from sources of ignition. Do not puncture or incinerate container. When using this product, keep away from face and mouth to avoid breathing in.

Inactive Ingredients

Alcohol, Benzyl Benzoate, Butane, Citral, Citronellol, Colloidal Gold, Geraniol, Glycerin, Hydroxycitronellal, Limonene, Linalool, Menthyl Lactate, Parfum, PPG-6-Decyltetradeceth-30, Propane, Sodium Polyacrylate, Water, Xanthan Gum

INDICATIONS AND USAGE

No Pain More Gain

Sport Strength

Pre & Post Workout

100% Vegan No Animal Testing

NPMG is • 100% vegan • Gluten-free • GMO-free • Free of paraben, paraffin and silicone oil • Made from spring water • Cruelty-free

Build muscle and get strong faster. NPMG Sport Strength is a superior pre-and post-workout spray optimized for bodybuilding and all strength related sports, endorsed by physiotherapists. The innovative crackling spray contains tiny bubbles. They burst on contact with the skin and release their unique properties. NPMG Sport Strength is cold at first, then warm. It can be used selectively, but also on large areas. It is made from the finest spring water. Its proprietary blend is loaded with minerals and electrolytes, powered by menthol, enhanced by colloidal gold and optimized with lemon and almond oil. NPMG Sport Strength penetrates deeply, absorbs quickly, moisturizes the skin and has a fresh and pleasant scent.The natural alternative with the advanced German formula starts to work on contact, penetrates deeply, absorbs quickly and has a fresh and pleasant scent.

NPMG Sport Strength is a product of

Lugus Group LLC, Buffalo, WY 82834, USA

NET WT 5.07 fl oz (150 ml)

Keep out of reach of children.